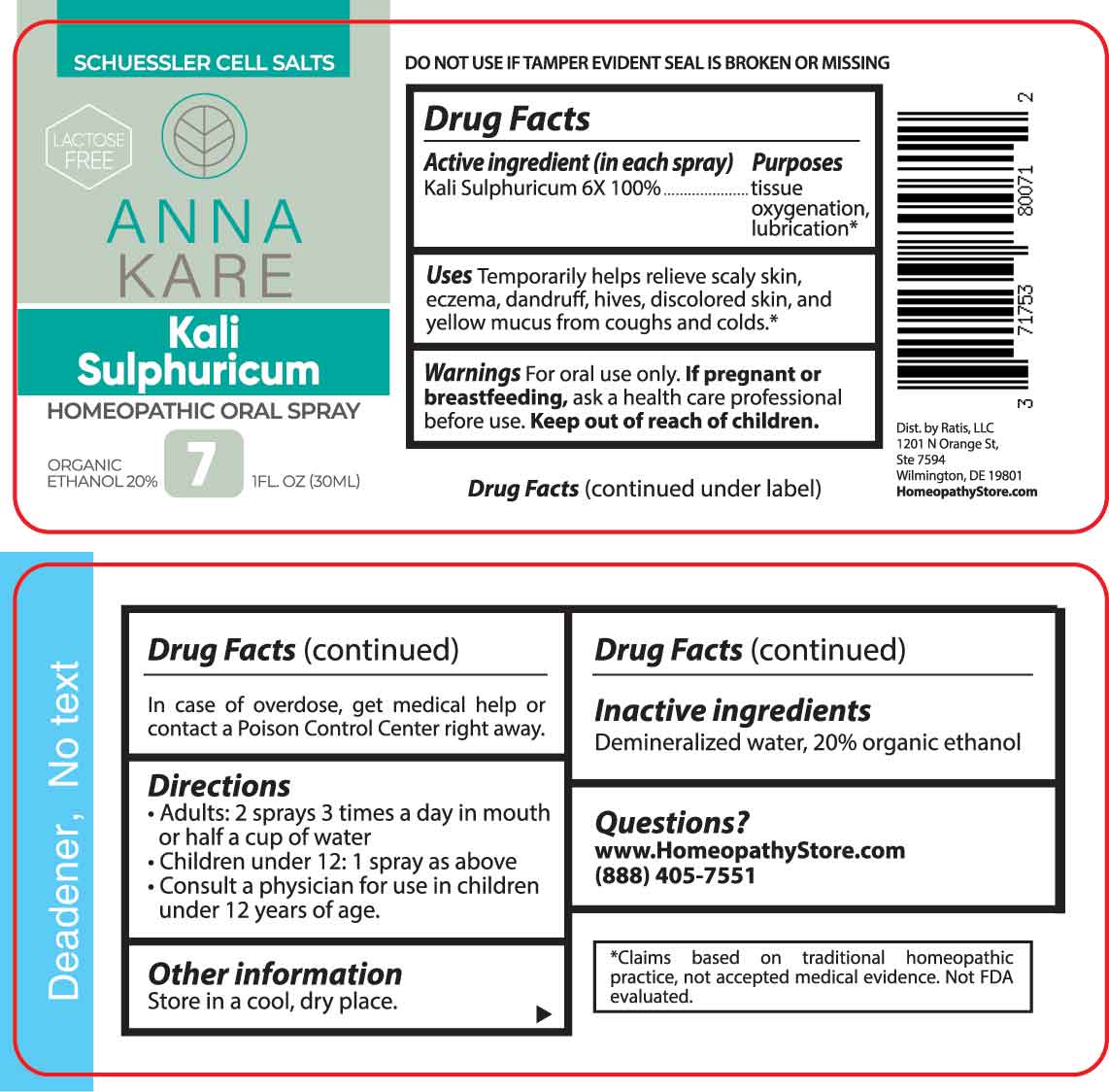 DRUG LABEL: Kali Sulphuricum
NDC: 71753-8007 | Form: SPRAY
Manufacturer: Ratis, LLC
Category: homeopathic | Type: HUMAN OTC DRUG LABEL
Date: 20230713

ACTIVE INGREDIENTS: POTASSIUM SULFATE 6 [hp_X]/1 mL
INACTIVE INGREDIENTS: WATER; ALCOHOL

DRUG FACTS:

ACTIVE INGREDIENT:

Kali Sulphuricum 6X 100%.

PURPOSES:

Kali Sulphuricum - tissue oxygenation, lubrication*

USES:

Temporarily helps relieve scaly skin, eczema, dandruff, hives, discolored skin, and yellow mucus from coughs and colds.*

*Claims based on traditional homeopathic practice, not accepted medical evidence. Not FDA evaluated.

WARNINGS:

For oral use only.

If pregnant or breast-feeding, ask a health care professional before use.

Keep out of reach of children. In case of overdose, get medical help or contact a Poison Control Center right away.

DO NOT USE IF TAMPER EVIDENT SEAL IS BROKEN OR MISSING

KEEP OUT OF REACH OF CHILDREN:

In case of overdose, get medical help or contact a Poison Control Center right away.

DIRECTIONS:

• Adults: 2 sprays 3 times a day in mouth or half a cup of water.

• Children under 12: 1 spray as above.

• Consult a physician for use in children under 12 years of age.

INACTIVE INGREDIENTS:

Demineralized water, 20% organic ethanol

QUESTIONS:

www.HomeopathyStore.com

(888) 405-7551

Dist. by Ratis, LLC

1201 N Orange St

Ste 7594

Wilmington, DE 19801

PACKAGE LABEL DISPLAY:

SCHUESSLER CELL SALTS

LACTOSE FREE

ANNA

KARE

Kali

Sulphuricum

HOMEOPATHIC ORAL SPRAY

1 FL. OZ (30ML)